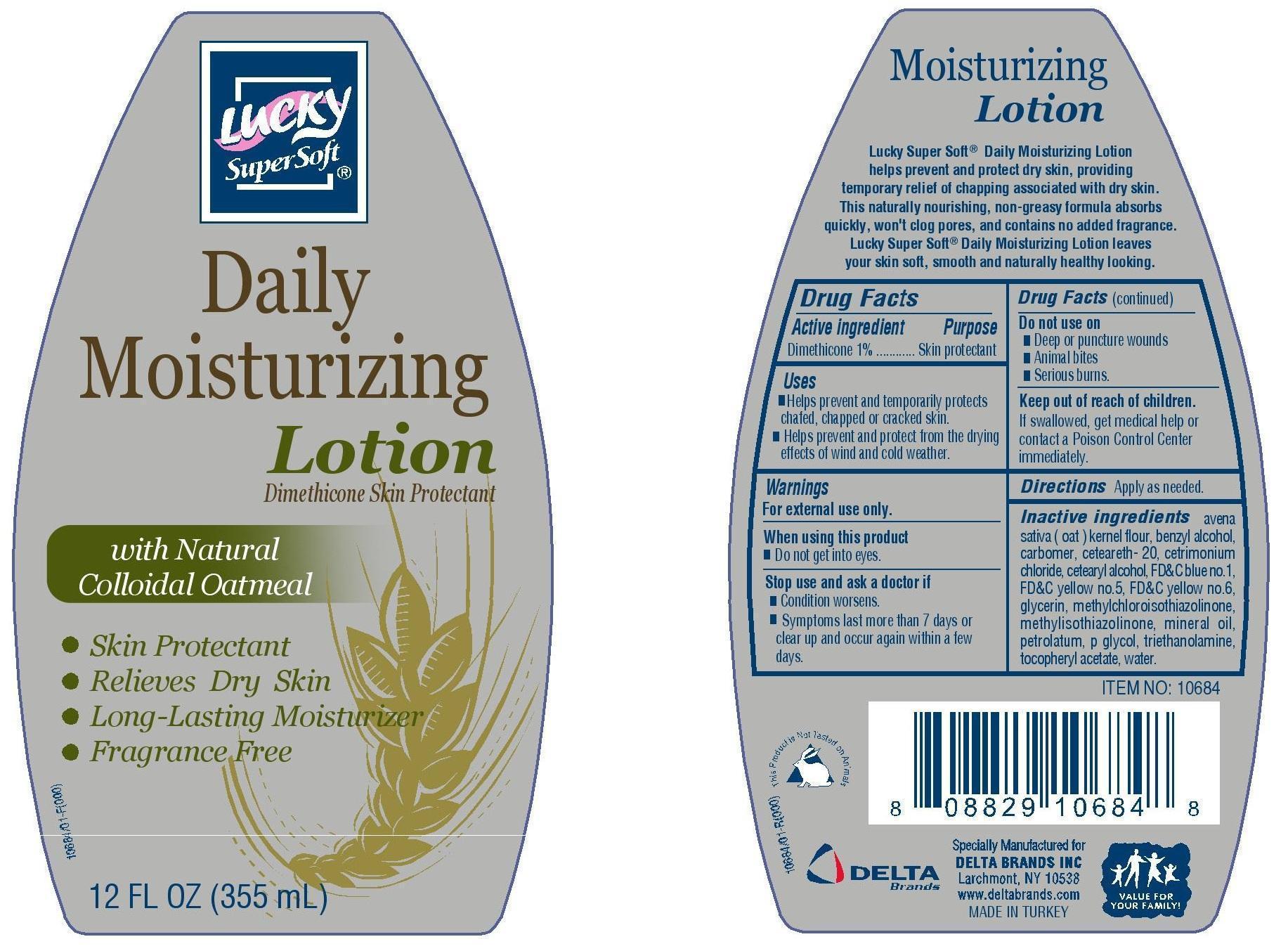 DRUG LABEL: Lucky
NDC: 20276-044 | Form: LOTION
Manufacturer: Delta Brands Inc
Category: otc | Type: HUMAN OTC DRUG LABEL
Date: 20230622

ACTIVE INGREDIENTS: DIMETHICONE 1 g/100 mL
INACTIVE INGREDIENTS: METHYLISOTHIAZOLINONE; MINERAL OIL; PETROLATUM; TROLAMINE; .ALPHA.-TOCOPHEROL ACETATE; WATER; AVENA SATIVA FLOWERING TOP; BENZYL ALCOHOL; POLYOXYL 20 CETOSTEARYL ETHER; CETOSTEARYL ALCOHOL; FD&C BLUE NO. 1; FD&C YELLOW NO. 5; FD&C YELLOW NO. 6; GLYCERIN; METHYLCHLOROISOTHIAZOLINONE

DRUG FACTS

Active Ingredient

Dimethicone 1%

Purpose

Skin protectant

Uses

■Helps prevent and temporarily protects chafed, chapped, or cracked skin

■Helps prevent and protect from the drying effects of wind and cold weather

Warnings

For external use only

When using this product

■Do not get into eyes

Stop use and ask a doctor if

■Condition worsens

■Symptoms last more than 7 days or clear up and occur again within a few days.

Do not use on

■Deep or puncture wounds

■Animal bites

■Serious burns

Keep out of reach of children

If swallowed, get medical help or contact a Poison Control Center immediately.

Directions

Apply as needed

Inactive ingredients

avena sativa (oat) kernel flour, benzyl alcohol, carbomer, ceteareth-20, cetrimonium chloride, cetearyl alcohol, FD&C blue no.1, FD&C yellow no.5, FD&C yellow no.6, glycerin, methylchloroisothiazolinone, methylisothiazolinone, mineral oil, petrolatum, p glycol, triethanolamine, tocopheryl acetate, water